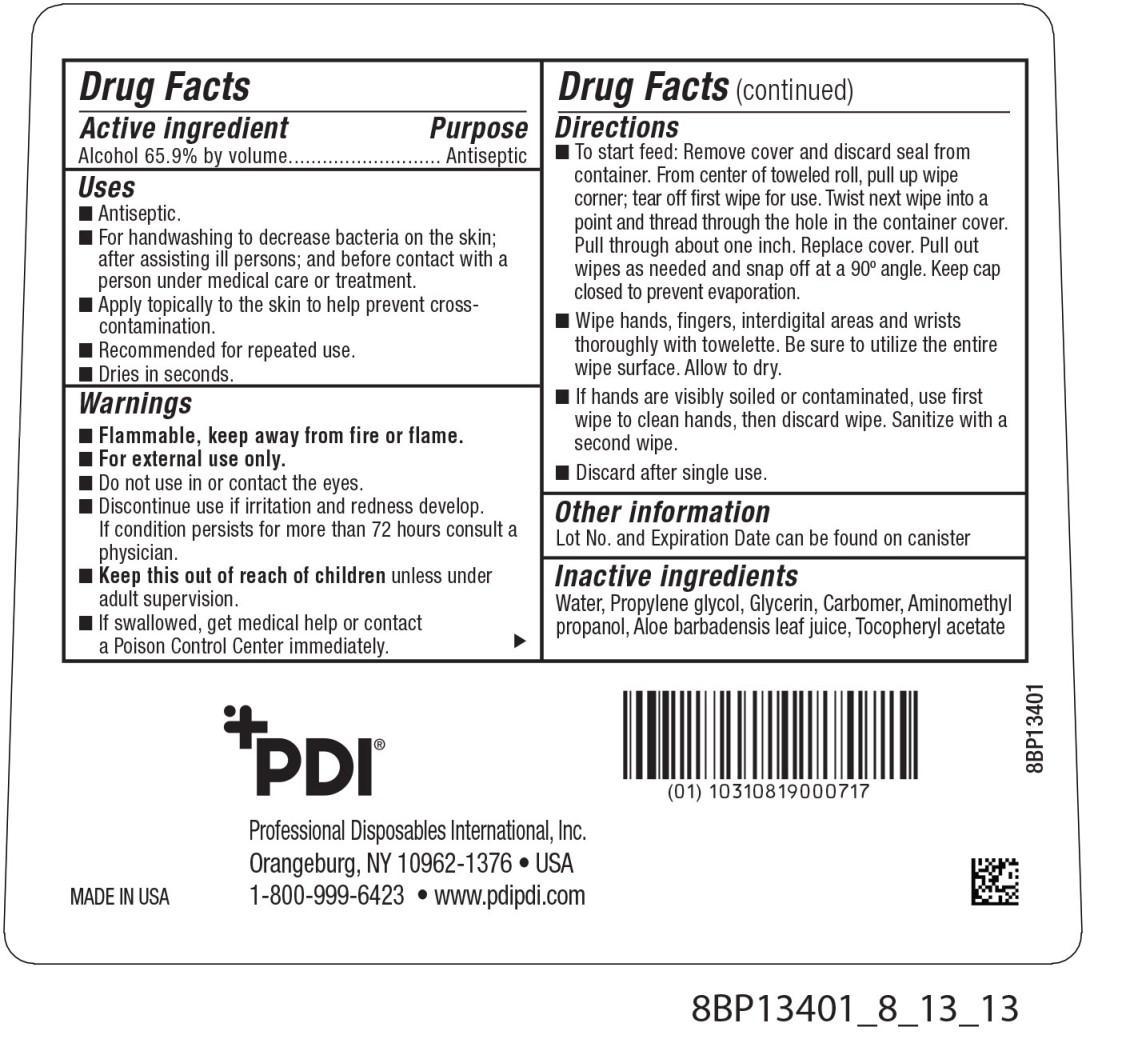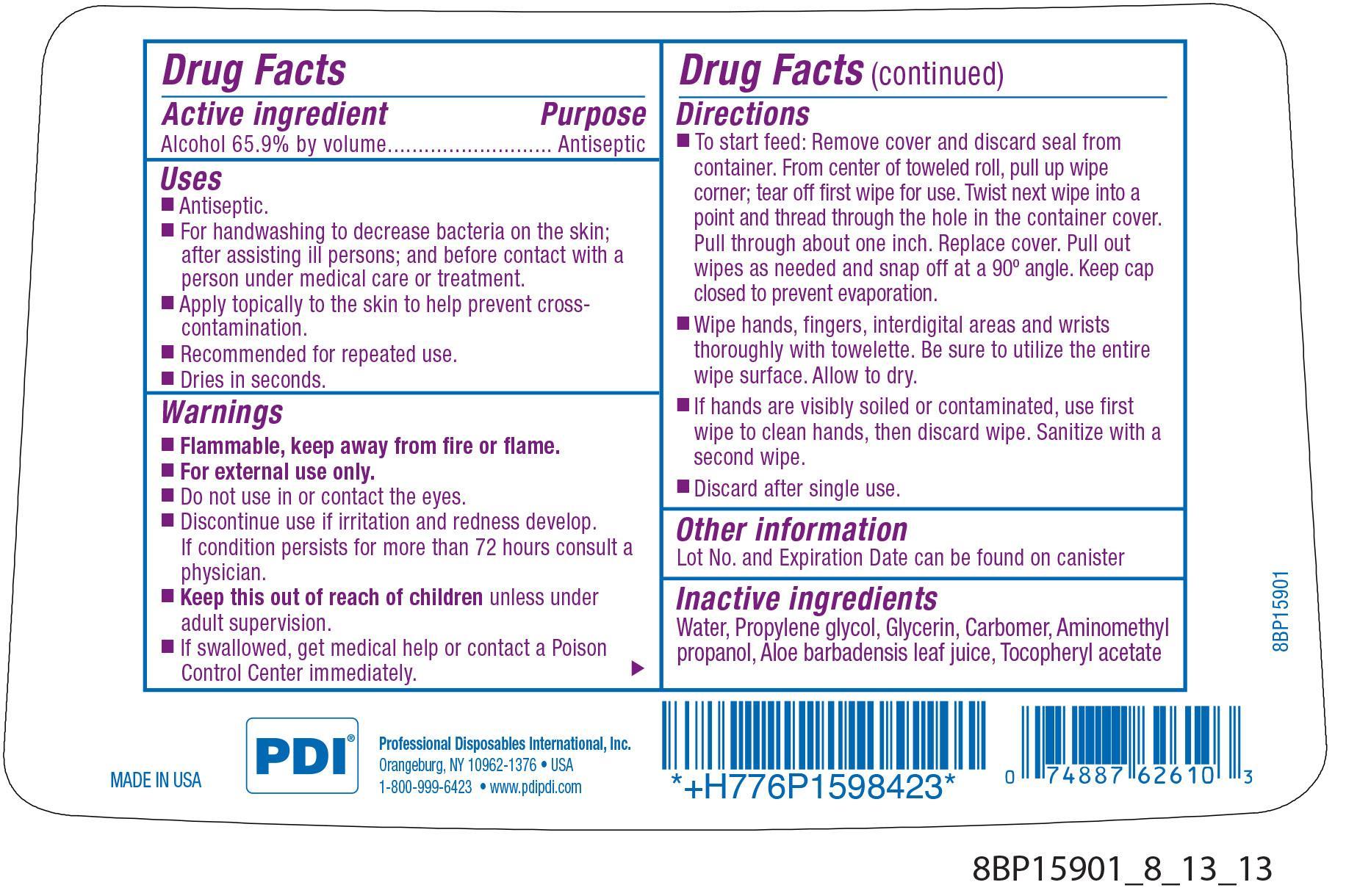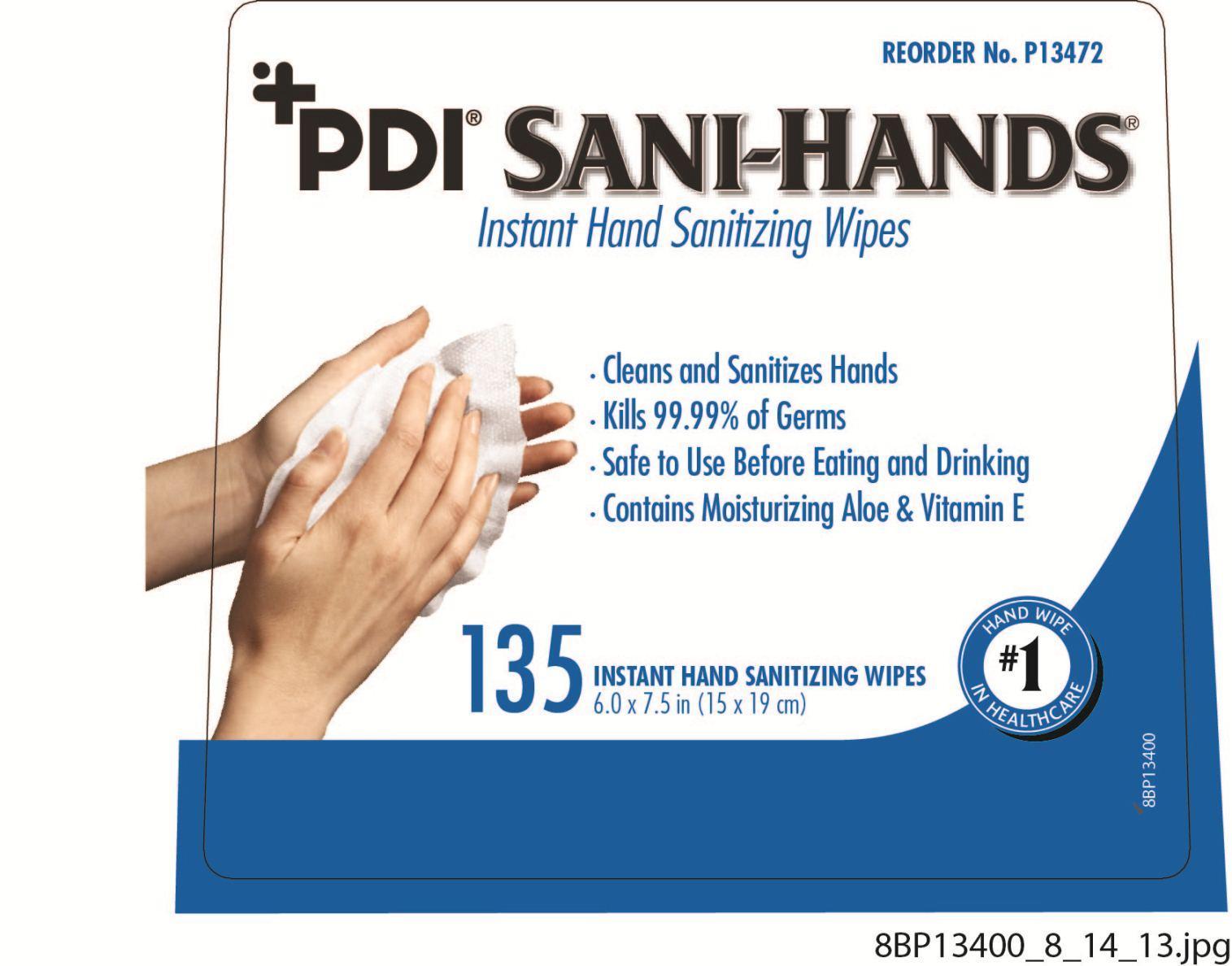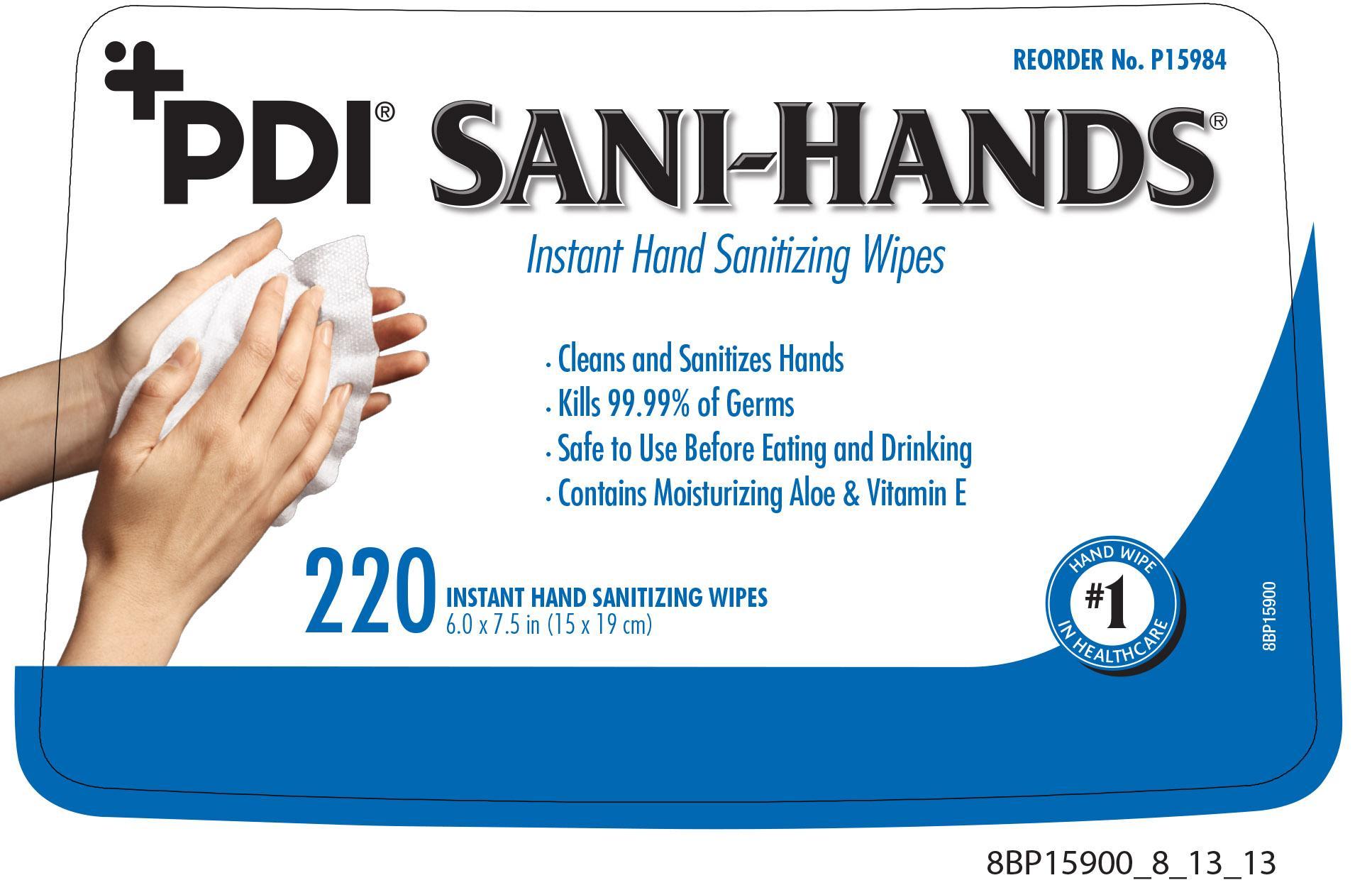 DRUG LABEL: PDI Sani-HandsInstant Hand Sani
NDC: 10819-5814 | Form: CLOTH
Manufacturer: Professional Disposables International, Inc.
Category: otc | Type: HUMAN OTC DRUG LABEL
Date: 20131121

ACTIVE INGREDIENTS: Alcohol 0.659 mL/1 mL
INACTIVE INGREDIENTS: WATER; PROPYLENE GLYCOL; GLYCERIN; CARBOMER HOMOPOLYMER TYPE C; AMINOMETHYL PROPANEDIOL; ALOE VERA LEAF; ALPHA-TOCOPHEROL ACETATE

PDI SANI-HANDS INSTANT HAND SANITIZING WIPES

Uses

- Antiseptic.
- For handwashing to decrease bacteria on the skin; after assisting ill persons; and before contact with a person under medical care or treatment.
- Apply topically to the skin to help prevent cross-contamination.
- Recommended for repeated use.
- Dries in seconds.

Warnings

- Flammable, keep away from fire or flame.
- For external use only.
- Do not use in or contact the eyes.
- Discontinue use if irritation and redness develop. If condition persist for more than 72 hours consult a physician.
- If swallowed, get medical help or contact a Poison Control Center immediately.

KEEP OUT OF REACH OF CHILDREN

- Keep this out of reach of children unless under adult supervision.

Directions

- To start feed: Remove cover and discard seal from container. From center of toweled roll, pull up wipe corner; tear off first wipe for use. Twist next wipe into a point and thread through the hole in the container cover. Pull through about one inch. Replace cover. Pull out wipes as needed and snap off at a 90o angle. Keep cap closed to prevent evaporation.
- Wipe hands, fingers, interdigital areas and wrists thoroughly with towelettes. Be sure to utilize the entire wipe surface. Allow to dry.
- If hands are visibly soiled or contaminated, use first wipe to clean hands, then discard wipe. Sanitize with a second wipe.
- Discard after single use.

Other information

Lot No. and Expiration Date can be found on canister

Dosage

If hands are visibly soiled or contaminated, use first wipe to clean hands, then discard wipe. Sanitize with a second wipe. Discard after single use.

Inactive ingredients

Water, Propylene Glycol, Glycerin, Carbomer, Aminometyl Propanol, Aloe Barbadensis Leaf Juice, Tocopheryl Acetate

Professional Disposables International, Inc.
Orangeburg, NY 10962-1376 - USA - 1-800-999-6423
www.pdipdi.com MADE IN USA

Principal Display Panel

PDI SANI-HANDS(R)
Instant Hand Sanitizing Wipes

- Cleans and Sanitizes Hands
- Kills 99.99% of Germs
- Safe to Use Before Eating and Drinking
- Contains Moisturizing Aloe and Vitamin E

#1 Hand Wipe in Healthcare

Front Canister Label 220 ct
Back Canister Label 220 ct
Front Canister Label 135 ct
Back Canister Label 135 ct

Active ingredient

Alcohol 65.9% by volume

Purpose

Antiseptic